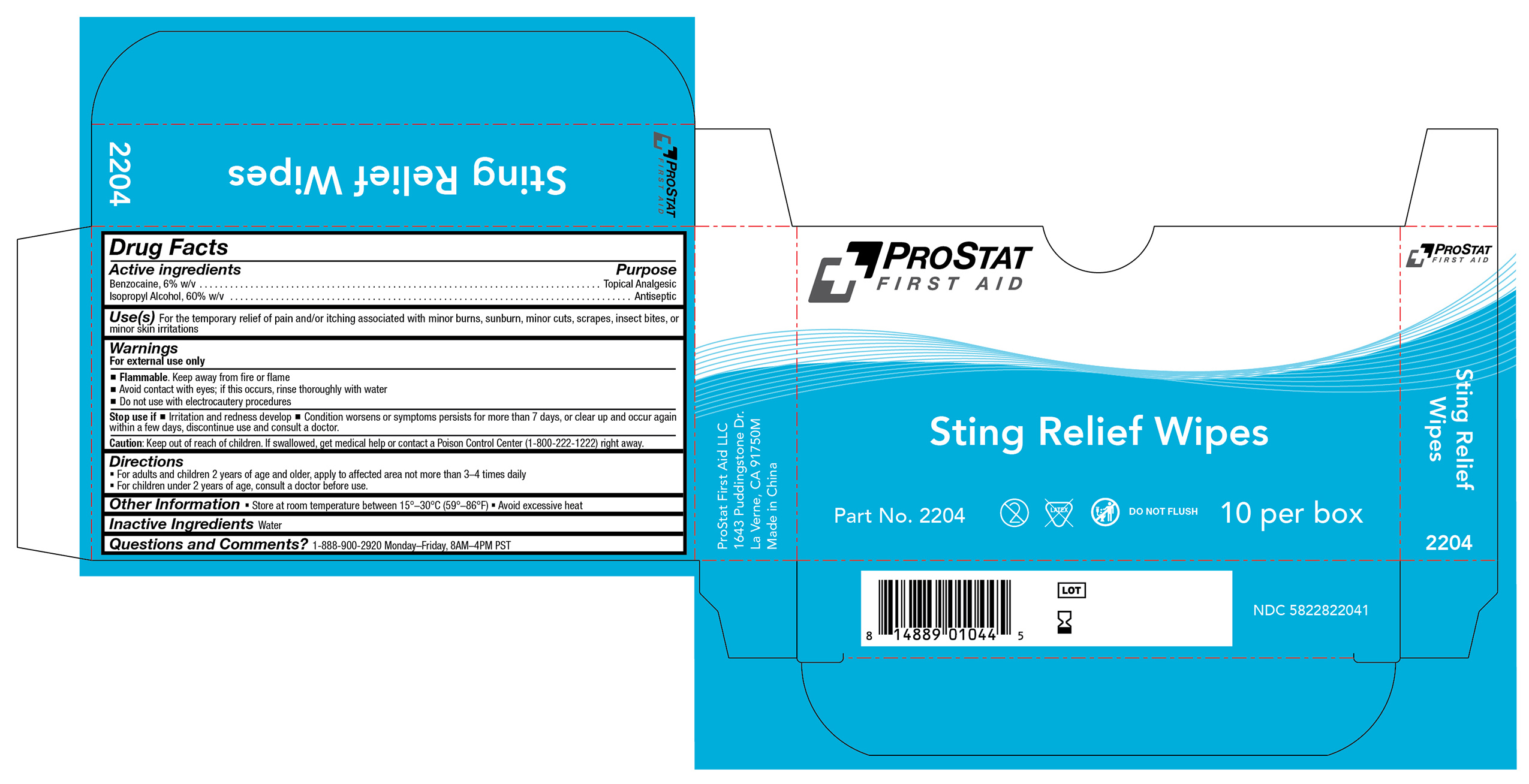 DRUG LABEL: Sting Relief Wipes
NDC: 58228-2204 | Form: SWAB
Manufacturer: ProStat First Aid LLC
Category: otc | Type: HUMAN OTC DRUG LABEL
Date: 20251215

ACTIVE INGREDIENTS: ISOPROPYL ALCOHOL 60 mg/100 mL; BENZOCAINE 6 mg/100 mL
INACTIVE INGREDIENTS: WATER

PS-2204

Active ingredients

Benzocaine, 6% w/v

Purpose

Topical Analgesic

Active Ingredient

Isopropyl Alcohol, 60% w/v

Purpose

Antiseptic

Use(s)

For the temporary relief of pain and/or itching associated with minor burns, sunburn, minor cuts, scrapes, insect bites, or minor skin irritations

Warnings

For External Use Only

Flammable. Keep away from fire or flame.

When using

• Avoid contact with eyes; if this occurs, rinse thoroughtly with water

Do not use

• With electrocautery procedures

Stop use if

• Irritation and redness develop

• Condition worsens or symptoms persist for more than 7 days, or clear up and occur again within a few day; discontinue use and consult a doctor

Keep out of reach of children

If swallowed, get medical help or contact a Poison Control Center (1-800-222-1222) right away.

Directions

• For adults and children 2 years of age and older, apply to affected area not more than 3-4 times daily.

• For children under 2 years of age, consult a doctor before use.

Other information

• Store at room temperature 15º-30ºC (59º-86ºF)

• Avoid excessive heat

Inactive Ingredients

Water

Questions and Comments?

1-888-900-2920 Monday-Friday, 8AM-4PM PST